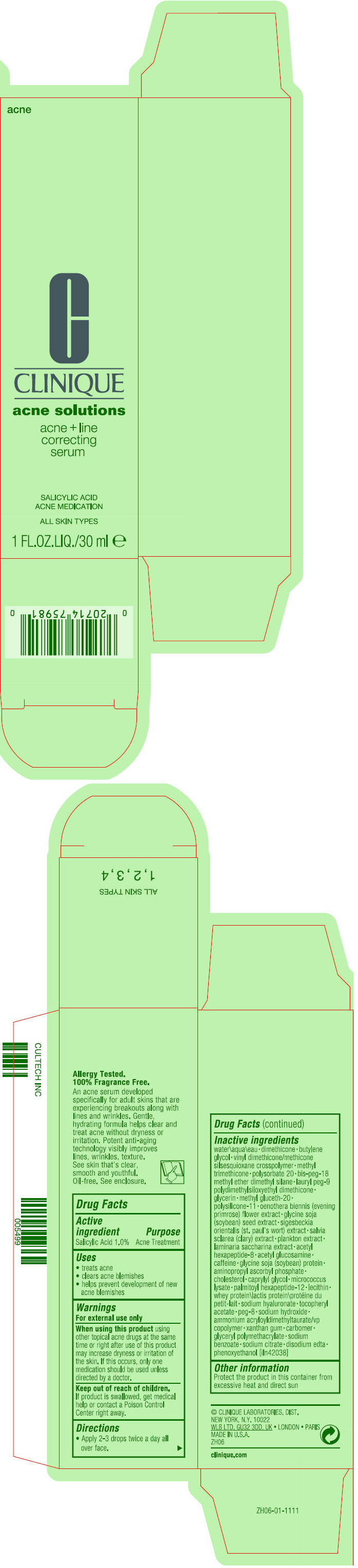 DRUG LABEL: ACNE AND LINE CORRECTING SERUM
NDC: 49527-053 | Form: LOTION
Manufacturer: CLINIQUE LABORATORIES LLC
Category: otc | Type: HUMAN OTC DRUG LABEL
Date: 20231005

ACTIVE INGREDIENTS: SALICYLIC ACID 10 mg/1 mL
INACTIVE INGREDIENTS: WATER; DIMETHICONE; BUTYLENE GLYCOL; METHYL TRIMETHICONE; POLYSORBATE 20; BIS-PEG-18 METHYL ETHER DIMETHYL SILANE; LAURYL PEG-9 POLYDIMETHYLSILOXYETHYL DIMETHICONE; GLYCERIN; METHYL GLUCETH-20; DIMETHICONE/VINYL DIMETHICONE CROSSPOLYMER (SOFT PARTICLE); OENOTHERA BIENNIS FLOWER; SOYBEAN; SACCHARINA LATISSIMA; ACETYL HEXAPEPTIDE-8; N-ACETYLGLUCOSAMINE; CAFFEINE; SOY PROTEIN; AMINOPROPYL ASCORBYL PHOSPHATE; CHOLESTEROL; CAPRYLYL GLYCOL; PALMITOYL HEXAPEPTIDE-12; WHEY; HYALURONATE SODIUM; .ALPHA.-TOCOPHEROL ACETATE; POLYETHYLENE GLYCOL 400; SODIUM HYDROXIDE; AMMONIUM ACRYLOYLDIMETHYLTAURATE/VP COPOLYMER; XANTHAN GUM; CARBOMER HOMOPOLYMER, UNSPECIFIED TYPE; SODIUM BENZOATE; SODIUM CITRATE, UNSPECIFIED FORM; EDETATE DISODIUM ANHYDROUS; PHENOXYETHANOL

ACNE SOLUTIONS ACNE AND LINE CORRECTING SERUM

Drug Facts

Active ingredient

Salicylic Acid 1.0%

Purpose

Acne Treatment

Uses

- treats acne
- clears acne blemishes
- helps prevent development of new acne blemishes

Warnings

For external use only

When using this product using other topical acne drugs at the same time or right after use of this product may increase dryness or irritation of the skin. If this occurs, only one medication should be used unless directed by a doctor.

Keep out of reach of children. If product is swallowed, get medical help or contact a Poison Control Center right away.

Directions

- Apply 2-3 drops twice a day all over face.

Inactive ingredients

water\aqua\eau • dimethicone • butylene glycol • vinyl dimethicone/methicone silsesquioxane crosspolymer • methyl trimethicone • polysorbate 20 • bis-peg-18 methyl ether dimethyl silane • lauryl peg-9 polydimethylsiloxyethyl dimethicone • glycerin • methyl gluceth-20 • polysilicone-11 • oenothera biennis (evening primrose) flower extract • glycine soja (soybean) seed extract • sigesbeckia orientalis (st. paul's wort) extract • salvia sclarea (clary) extract • plankton extract • laminaria saccharina extract • acetyl hexapeptide-8 • acetyl glucosamine • caffeine • gylcine soja (soybean) protein • aminopropyl ascorbyl phosphate • cholesterol • caprylyl glycol • micrococcus lysate • palmitoyl hexapeptide-12 • lecithin • whey protein\lactis protein\protéine du petit-lait • sodium hyaluronate • tocopheryl acetate • peg-8 • sodium hydroxide • ammonium acryloyldimethyltaurate/vp copolymer • xanthan gum • carbomer • glyceryl polymethacrylate • sodium benzoate • sodium citrate • disodium edta • phenoxyethanol [iln42038]

Other information

Protect the product in this container from excessive heat and direct sun

© CLINIQUE LABORATORIES, DIST.
NEW YORK, N.Y. 10022

PRINCIPAL DISPLAY PANEL - 30 ml Bottle Carton

acne

C

CLINIQUE

acne solutions

acne + line
correcting
serum

SALICYLIC ACID
ACNE MEDICATION

ALL SKIN TYPES

1 FL.OZ.LIQ./30 ml e